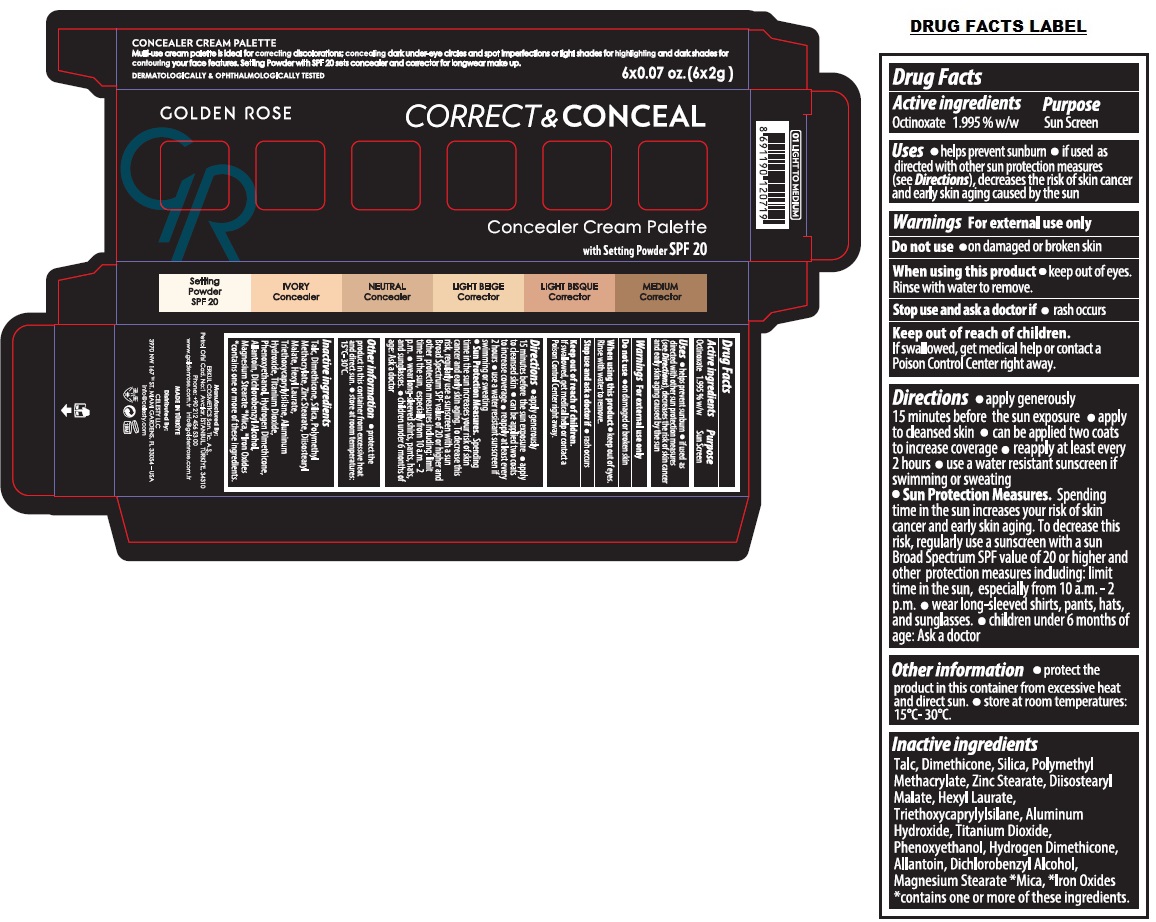 DRUG LABEL: GOLDEN ROSE CORRECT AND CONCEAL Concealer Cream Palette
NDC: 82715-120 | Form: POWDER
Manufacturer: ERKUL KOZMETIK SANAYI VE TICARET ANONIM SIRKETI
Category: otc | Type: HUMAN OTC DRUG LABEL
Date: 20250806

ACTIVE INGREDIENTS: OCTINOXATE 1.995 g/100 g
INACTIVE INGREDIENTS: TALC; DIMETHICONE, UNSPECIFIED; SILICON DIOXIDE; POLY(METHYL METHACRYLATE; 450000 MW); ZINC STEARATE; DIISOSTEARYL MALATE; HEXYL LAURATE; TRIETHOXYCAPRYLYLSILANE; ALUMINUM HYDROXIDE; TITANIUM DIOXIDE; PHENOXYETHANOL; HYDROGEN DIMETHICONE (13 CST); ALLANTOIN; DICHLOROBENZYL ALCOHOL; MAGNESIUM STEARATE; MICA; FERRIC OXIDE RED

GOLDEN ROSE CORRECT&CONCEAL Concealer Cream Palette

Active ingredients

Octinoxate 1.995% w/w

Purpose

SunScreen

Uses

• helps prevent sunburn • if used as directed with other sun protection measures (see Directions), decreases the risk of skin cancer and early skin aging caused by the sun

Warnings

For external use only

Do not use • on damaged or broken skin

When using this product • keep out of eyes. Rinse with water to remove.

Stop use and ask a doctor if • rash occurs

Keep out of reach of children.
If swallowed, get medical help or contact a Poison Control Center right away.

Directions

• apply generously 15 minutes before the sun exposure • apply to cleansed skin • can be applied two coats to increase coverage • reapply at least every 2 hours • use a water resistant sunscreen if swimming or sweating
• Sun Protection Measures. Spending time in the sun increases your risk of skin cancer and early skin aging. To decrease this risk, regularly use a sunscreen with a sun Broad Spectrum SPF value of 20 or higher and other protection measures including: limit time in the sun, especially from 10 a.m.– 2 p.m. • wear long-sleeved shirts, pants, hats, and sunglasses. • children under 6 months of age: Ask a doctor

Other information

• protect the product in this container from excessive heat and direct sun. • store at room temperatures: 15°C-30°C.

Inactive ingredients

Talc, Dimethicone, Silica, Polymethyl Methacrylate, Zinc Stearate, Diisostearyl Malate, Hexyl Laurate, Triethoxycaprylylsilane, Aluminum Hydroxide, Titanium Dioxide, Phenoxyethanol, Hydrogen Dimethicone, Allantoin, Dichlorobenzyl Alcohol, Magnesium Stearate, *Mica, *Iron Oxides
*contains one or more of these ingredients.

Multi-use cream palette is ideal for correcting discolorations; concealing dark under-eye circles and spot imperfections or light shades for highlighting and dark shades for contouring your face features. Setting Powder with SPF 20 sets concealer and corrector for longwear make up.

DERMATOLOGICALLY & OPHTHALMOLOGICALLY TESTED

Setting Powder SPF 20
IVORY Concealer
NEUTRAL Concealer
LIGHT BEIGE Corrector
LIGHT BISQUE Corrector
MEDIUM Corrector

Manufactured By:
ERKUL COSMETICS San. Tic. A.S.,
Petrol Ofisi Cad. No:1 Avcılar, ÍSTANBUL, TÜRKÍYE, 34310
Phone: +90 212 456 53 00

www.goldenrose.com.tr info@goldenrose.com.tr

MADE IN TÜRKÍYE

Distributed By:
CELESTY LLC
3970 NW 167TH ST. MIAMI GARDENS, FL 33054-USA
info@celesty.com